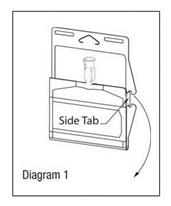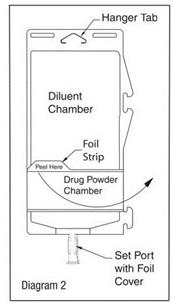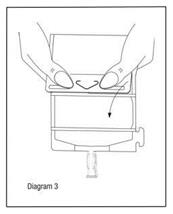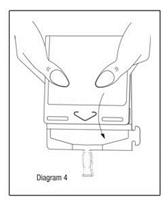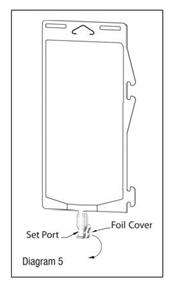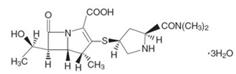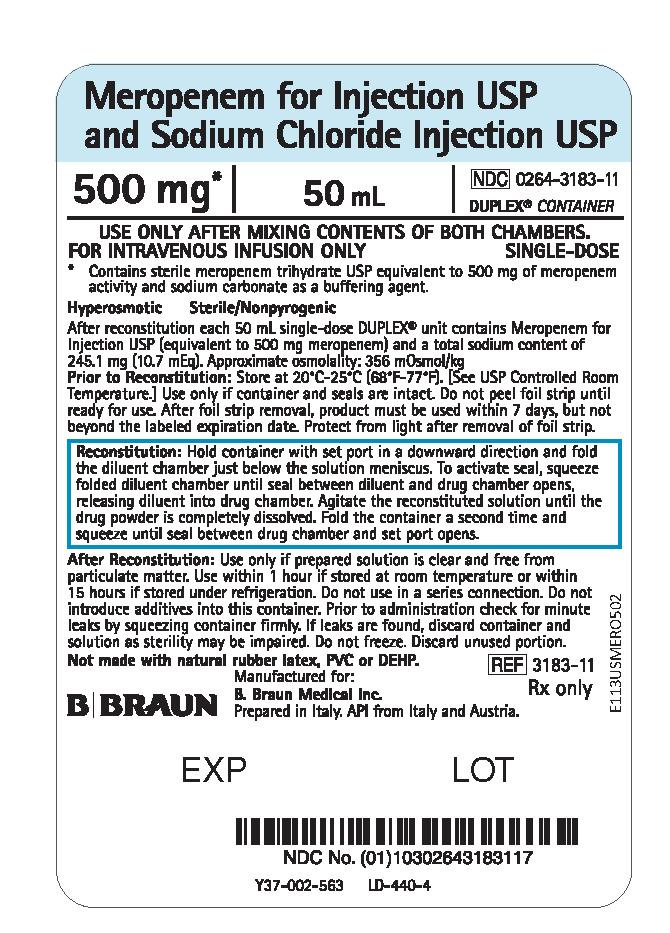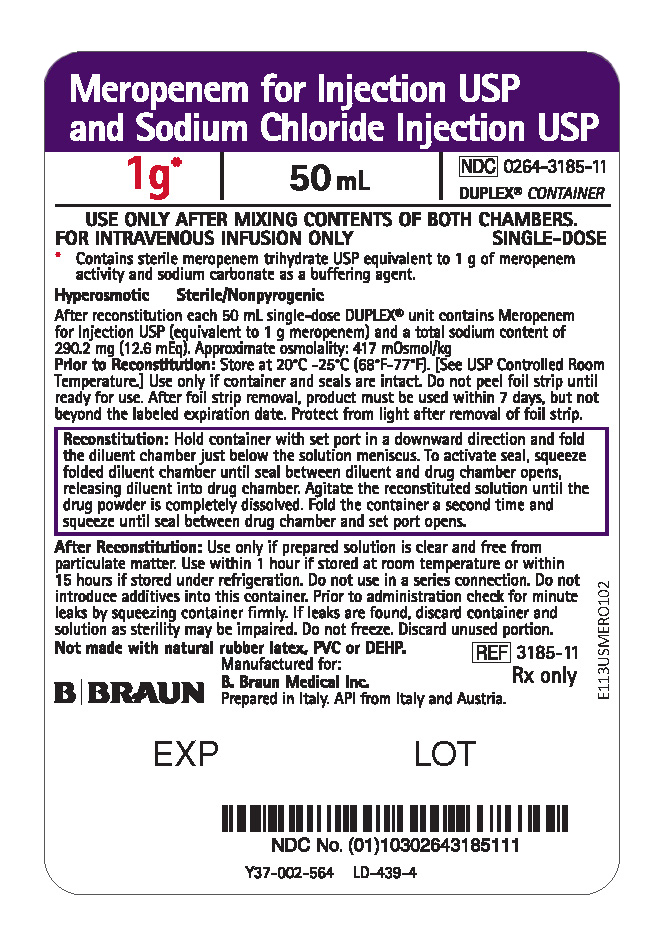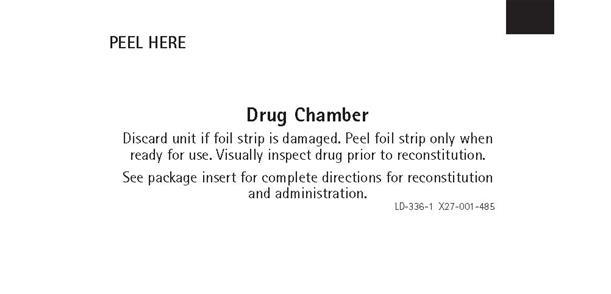 DRUG LABEL: Meropenem and Sodium Chloride
NDC: 0264-3183 | Form: INJECTION, SOLUTION
Manufacturer: B. Braun Medical Inc.
Category: prescription | Type: HUMAN PRESCRIPTION DRUG LABEL
Date: 20250805

ACTIVE INGREDIENTS: MEROPENEM 500 mg/50 mL
INACTIVE INGREDIENTS: SODIUM CHLORIDE 0.45 g/50 mL; SODIUM CARBONATE; WATER

HIGHLIGHTS OF PRESCRIBING INFORMATION

These highlights do not include all the information needed to use MEROPENEM FOR INJECTION AND SODIUM CHLORIDE INJECTION safely and effectively. See full prescribing information for MEROPENEM FOR INJECTION AND SODIUM CHLORIDE INJECTION.
MEROPENEM for injection AND SODIUM CHLORIDE injection, for intravenous use
Initial U.S. Approval: 1996

RECENT MAJOR CHANGES

Warnings and Precautions, Rhabdomyolysis (5.3) 12/2024

1 INDICATIONS AND USAGE

Meropenem for Injection and Sodium Chloride Injection is a penem antibacterial indicated for the treatment of:

- Complicated skin and skin structure infections (adult patients and pediatric patients 3 months of age and older requiring the full adult dose only). (1.1)
- Complicated intra-abdominal infections (adult patients and pediatric patients 3 months of age and older requiring the full adult dose only). (1.2)
- Bacterial meningitis (pediatric patients 3 months of age and older requiring the full adult dose only). (1.3)

To reduce the development of drug-resistant bacteria and maintain the effectiveness of Meropenem for Injection and Sodium Chloride Injection and other antibacterial drugs, Meropenem for Injection and Sodium Chloride Injection should only be used to treat or prevent infections that are proven or strongly suspected to be caused by bacteria.

2 DOSAGE AND ADMINISTRATION

Use this formulation of meropenem only in patients who require the entire 500 mg or 1 gram dose and not any fraction thereof. (2.1)

- 500 mg every 8 hours by intravenous infusion over 15 to 30 minutes for complicated skin and skin structure infections (cSSSI) for adult patients. When treating infections caused by Pseudomonas aeruginosa, a dose of 1 gram every 8 hours is recommended (2.1).
- 1 gram every 8 hours by intravenous infusion over 15 to 30 minutes for intra-abdominal infections for adult patients. (2.1)
- Dosage should be reduced in adult patients with renal impairment. If less than a full dose (1 gram or 500 mg) is required, an alternative formulation should be used to avoid risk of overdose. (2.2)

Recommended Meropenem for Injection Dosage Schedule for Adult Patients with Renal Impairment
Creatinine Clearance (mL/min) | Dose (dependent on type of infection) | Dosing Interval
greater than 50 | Recommended dose (500 mg cSSSI and 1 gram Intra-abdominal infection) | Every 8 hours
26-50 | Recommended dose | Every 12 hours
10-25 | One-half recommended dose | Every 12 hours
less than 10 | One-half recommended dose | Every 24 hours

Meropenem for Injection and Sodium Chloride Injection in the DUPLEX® Container is designed to deliver a 500 mg or 1 gram dose of Meropenem. To prevent unintentional overdose, this product should not be used in pediatric patients who require less than the full adult dose of Meropenem. Meropenem is not to be used in pediatric patients aged less than three months. There is no experience in pediatric patients with renal impairment.

- Pediatric patients 3 months of age and older. (2.3)

Recommended Meropenem for Injection Dosage Schedule for Pediatric Patients with Normal Renal Function
Type of Infection | Dose (mg/kg) | Up to a Maximum Dose | Dosing Interval
Complicated skin and skin structure [20 mg/kg (or 1 gram for pediatric patients weighing over 50 kg) every 8 hours is recommended when treating complicated skin and skin structure infections caused by P. aeruginosa (2.3).] | 10 | 500 mg | Every 8 hours
Intra-abdominal | 20 | 1 gram | Every 8 hours
Meningitis | 40 | 2 grams | Every 8 hours
- Intravenous infusion is to be given over approximately 15 to 30 minutes.
- There is no experience in pediatric patients with renal impairment.

3 DOSAGE FORMS AND STRENGTHS

Single-dose DUPLEX® Container consisting of:

- 500 mg Meropenem for Injection and 50 mL Sodium Chloride Injection 0.9% (3)
- 1 gram Meropenem for Injection and 50 mL Sodium Chloride Injection 0.9% (3)

4 CONTRAINDICATIONS

- Known hypersensitivity to product components or anaphylactic reactions to beta-lactams. (4)
- Contraindicated where the administration of sodium or chloride could be clinically detrimental. (4)

5 WARNINGS AND PRECAUTIONS

- Serious and occasionally fatal hypersensitivity (anaphylactic) reactions have been reported in patients receiving beta-lactams. (5.1)
- Severe cutaneous adverse reactions have been reported in patients receiving meropenem intravenous. Discontinue meropenem immediately if patients experience these signs and symptoms and consider alternative treatment. (5.2)
- Rhabdomyolysis: If signs or symptoms of rhabdomyolysis are observed, discontinue Meropenem for Injection and Sodium Chloride Injection and initiate appropriate therapy. (5.3)
- Seizures and other adverse CNS experiences have been reported during treatment. (5.4)
- Co-administration of Meropenem for Injection with valproic acid or divalproex sodium reduces the serum concentration of valproic acid potentially increasing the risk of breakthrough seizures. (5.5, 7.2)
- Clostridioides difficile-associated diarrhea (ranging from mild diarrhea to fatal colitis) has been reported. Evaluate if diarrhea occurs. (5.6)
- In patients with renal dysfunction, thrombocytopenia has been observed. (5.9)
- Solutions containing sodium ions should be used with great care, if at all, in patients where the administration of sodium could be detrimental. (5.11)

6 ADVERSE REACTIONS

Most common adverse reactions (greater than or equal to 2%) are: headache, nausea, constipation, diarrhea, anemia, vomiting, and rash (6.1)

To report SUSPECTED ADVERSE REACTIONS, contact B. Braun Medical Inc. at 1-800-854-6851 or FDA at 1-800-FDA-1088 or www.fda.gov/medwatch.

7 DRUG INTERACTIONS

- Co-administration of Meropenem for Injection with probenecid inhibits renal excretion of meropenem and is therefore not recommended. (7.1)
- The concomitant use of Meropenem and valproic acid or divalproex sodium is generally not recommended. Antibacterial drugs other than carbapenems should be considered to treat infections in patients whose seizures are well controlled on valproic acid or divalproex sodium. (5.5, 7.2)

8 USE IN SPECIFIC POPULATIONS

- Pediatric use: Meropenem for Injection and Sodium Chloride Injection should not be used in pediatric patients who require less than the full adult dose of meropenem. (8.4)
- Renal Impairment: Dose adjustment is necessary, if creatinine clearance is 50 mL/min or less. (2.2, 8.6)

FULL PRESCRIBING INFORMATION

1 INDICATIONS AND USAGE

1.1 Complicated Skin and Skin Structure Infections (Adult Patients and Pediatric Patients 3 Months of age and older requiring the full adult dose only)

Meropenem for Injection and Sodium Chloride Injection is indicated for the treatment of complicated skin and skin structure infections (cSSSI) due to Staphylococcus aureus (methicillin-susceptible isolates only), Streptococcus pyogenes, Streptococcus agalactiae, viridans group streptococci, Enterococcus faecalis (vancomycin-susceptible isolates only), Pseudomonas aeruginosa, Escherichia coli, Proteus mirabilis, Bacteroides fragilis, and Peptostreptococcus species.

1.2 Complicated Intra-abdominal Infections (Adult Patients and Pediatric Patients 3 Months of age and older requiring the full adult dose only)

Meropenem for Injection and Sodium Chloride Injection is indicated for the treatment of complicated appendicitis and peritonitis caused by viridans group streptococci, Escherichia coli, Klebsiella pneumoniae, Pseudomonas aeruginosa, Bacteroides fragilis, B. thetaiotaomicron, and Peptostreptococcus species.

1.3 Bacterial Meningitis (Pediatric Patients 3 Months of age and older requiring the full adult dose only)

Meropenem for Injection and Sodium Chloride Injection is indicated for the treatment of bacterial meningitis caused by Haemophilus influenzae, Neisseria meningitidis and penicillin-susceptible isolates of Streptococcus pneumoniae.

Meropenem has been found to be effective in eliminating concurrent bacteremia in association with bacterial meningitis.

For information regarding use in pediatric patients (3 months of age and older) [see Indications and Usage (1.1), (1.2) or (1.3); Dosage and Administration (2.3), and Adverse Reactions (6.1)].

1.4 Usage

To reduce the development of drug-resistant bacteria and maintain the effectiveness of Meropenem for Injection and Sodium Chloride Injection and other antibacterial drugs, Meropenem for Injection and Sodium Chloride Injection should only be used to treat or prevent infections that are proven or strongly suspected to be caused by susceptible bacteria. When culture and susceptibility information are available, they should be considered in selecting or modifying antibacterial therapy. In the absence of such data, local epidemiology and susceptibility patterns may contribute to the empiric selection of therapy.

2 DOSAGE AND ADMINISTRATION

2.1 Adult Patients

Meropenem for Injection and Sodium Chloride Injection in the DUPLEX® Container should be used only in patients who require the entire 500 mg or 1 gram dose and not any fraction thereof. The recommended dose of Meropenem for Injection and Sodium Chloride Injection is 500 mg given every 8 hours for skin and skin structure infections and 1 gram given every 8 hours for intra-abdominal infections. When treating complicated skin and skin structure infections caused by P. aeruginosa, a dose of 1 gram every 8 hours is recommended.

Meropenem for Injection and Sodium Chloride Injection should be administered by intravenous infusion over approximately 15 to 30 minutes.

2.2 Use in Adult Patients with Renal Impairment

Dosage should be reduced in patients with creatinine clearance of 50 mL/min or less. (See dosing table below.)

Dosage should be reduced in renal failure if less than a full dose (1 gram or 500 mg) is required and an alternative formulation should be used to avoid risk of overdose.

When only serum creatinine is available, the following formula (Cockcroft and Gault equation)^1 may be used to estimate creatinine clearance.

Males: Creatinine Clearance (mL/min) =

Weight (kg) x (140 - age)

72 x serum creatinine (mg/dL)

Females: 0.85 x above value

Table 1: Recommended Meropenem for Injection Dosage Schedule for Adult Patients With Renal Impairment

Creatinine Clearance (mL/min) | Dose (dependent on type of infection) | Dosing Interval
greater than 50 | Recommended dose (500 mg cSSSI and 1 gram Intra-abdominal infection) | Every 8 hours
26-50 | Recommended dose | Every 12 hours
10-25 | One-half recommended dose | Every 12 hours
less than 10 | One-half recommended dose | Every 24 hours

There is inadequate information regarding the use of meropenem for injection in patients on hemodialysis or peritoneal dialysis.

2.3 Use in Pediatric Patients (3 Months of age and older only)

- Meropenem for Injection and Sodium Chloride Injection in the DUPLEX® Container is designed to deliver a 500 mg or 1 gram dose of meropenem. To prevent unintentional overdose, this product should not be used in pediatric patients who require less than the full adult dose of meropenem. Meropenem is not to be used in pediatric patients aged less than three months. For pediatric patients 3 months of age and older, the Meropenem for Injection and Sodium Chloride Injection dose is 10 mg/kg, 20 mg/kg or 40 mg/kg every 8 hours (maximum dose is 2 grams every 8 hours), depending on the type of infection (cSSSI, cIAI, intra-abdominal infection or meningitis). See dosing table 2 below. [see Use in Specific Populations (8.4)].
- For pediatric patients weighing over 50 kg administer Meropenem for Injection and Sodium Chloride Injection at a dose of 500 mg every 8 hours for cSSSI, 1 gram every 8 hours for cIAI and 2 grams every 8 hours for meningitis.
- Administer Meropenem for Injection and Sodium Chloride Injection as an intravenous infusion over approximately 15 minutes to 30 minutes.

Table 2: Recommended Meropenem for Injection Dosage Schedule for Pediatric Patients With Normal Renal Function

Type of Infection | Dose (mg/kg) | Up to a Maximum Dose | Dosing Interval
Complicated Skin and Skin Structure Infections | 10 | 500 mg | Every 8 hours
Complicated Intra-abdominal Infections | 20 | 1 gram | Every 8 hours
Meningitis | 40 | 2 grams | Every 8 hours

There is no experience in pediatric patients with renal impairment.

When treating cSSSI caused by P. aeruginosa, a dose of 20 mg/kg (or 1 gram for pediatric patients weighing over 50 kg) every 8 hours is recommended.

2.4 Preparation and Administration of Meropenem for Injection and Sodium Chloride Injection in DUPLEX® Container

Important Administration Instructions

- Do not use in series connections. Such use would result in air embolism due to residual air being drawn from the primary container before administration of the fluid from the secondary container is complete. If administration is controlled by a pumping device, care must be taken to discontinue pumping action before the container runs dry or air embolism may result.
- Do not introduce additives into the DUPLEX® Container.
- Administer Meropenem for Injection and Sodium Chloride Injection intravenously over approximately 15 to 30 minutes.

This reconstituted solution is for intravenous use only.

Parenteral drug products should be inspected visually for particulate matter and discoloration prior to administration.

Use only if solution is clear and container and seals are intact.

DUPLEX® Container Storage

- To avoid inadvertent activation, the DUPLEX® Container should remain in the folded position until activation is intended.

Patient Labeling and Drug Powder/Diluent Inspection

- Apply patient-specific label on foil side of container. Use care to avoid activation. Do not cover any portion of foil strip with patient label.
- Unlatch side tab and unfold DUPLEX® Container (see Diagram 1).

- Visually inspect diluent chamber for particulate matter.
- Use only if container and seals are intact.
- To inspect the drug powder for foreign matter or discoloration, peel foil strip from drug chamber (see Diagram 2).

- Protect from light after removal of foil strip.

Note: If foil strip is removed, the container should be re-folded and the side tab latched until ready to activate. The product must then be used within 7 days at room temperature, but not beyond the labeled expiration date.

Reconstitution (Activation)

- Do not use directly after storage by refrigeration, allow the product to equilibrate to room temperature before patient use.
- Unfold the DUPLEX® Container and point the set port in a downward direction. Starting at the hanger tab end, fold the DUPLEX® Container just below the diluent meniscus trapping all air above the fold. To activate, squeeze the folded diluent chamber until the seal between the diluent and powder opens, releasing diluent into the drug powder chamber (see Diagram 3).

- Agitate the liquid-powder mixture until the drug powder is completely dissolved.

Note: Following reconstitution (activation), product must be used within 1 hour if stored at room temperature or within 15 hours if stored under refrigeration.

Administration

- Visually inspect the reconstituted solution for particulate matter.
- Point the set port in a downwards direction. Starting at the hanger tab end, fold the DUPLEX® Container just below the solution meniscus trapping all air above the fold. Squeeze the folded DUPLEX® Container until the seal between reconstituted drug solution and set port opens, releasing liquid to set port (see Diagram 4).

- Prior to attaching the IV set, check for minute leaks by squeezing container firmly. If leaks are found, discard container and solution as sterility may be compromised.
- Using aseptic technique, peel foil cover from the set port and attach sterile administration set (see Diagram 5).

- Refer to directions for use accompanying the administration set.
- Discard unused portion.

2.5 Compatibility

Compatibility of Meropenem for Injection and Sodium Chloride Injection with other drugs has not been established. Meropenem for Injection and Sodium Chloride Injection should not be mixed with or physically added to solutions containing other drugs.

2.6 Stability and Storage

Freshly prepared solutions of Meropenem for Injection and Sodium Chloride Injection should be used. Following reconstitution (activation) in the DUPLEX® Container, the product maintains satisfactory potency for 1 hour at up to 25ºC (77ºF) or for 15 hours at up to 5ºC (41ºF). Solutions of intravenous Meropenem for Injection and Sodium Chloride Injection should not be frozen.

3 DOSAGE FORMS AND STRENGTHS

Single-dose DUPLEX® (Dual-chamber) container:

- 500 mg meropenem for injection USP (as a blend of sterile meropenem trihydrate USP and sterile sodium carbonate USP/NF) and 50 mL of sodium chloride injection USP
- 1 gram meropenem for injection USP (as a blend of sterile meropenem trihydrate USP and sterile sodium carbonate USP/NF) and 50 mL of sodium chloride injection USP

4 CONTRAINDICATIONS

Meropenem for Injection and Sodium Chloride Injection is contraindicated in patients with known hypersensitivity to any component of this product or to other drugs in the same class or in patients who have demonstrated anaphylactic reactions to beta-lactams.

5 WARNINGS AND PRECAUTIONS

5.1 Hypersensitivity Reactions

Serious and occasionally fatal hypersensitivity (anaphylactic) reactions have been reported in patients receiving therapy with beta-lactams. These reactions are more likely to occur in individuals with a history of sensitivity to multiple allergens.

There have been reports of individuals with a history of penicillin hypersensitivity who have experienced severe hypersensitivity reactions when treated with another beta-lactam. Before initiating therapy with Meropenem for Injection and Sodium Chloride Injection, it is important to inquire about previous hypersensitivity reactions to penicillins, cephalosporins, other beta-lactams, and other allergens. If an allergic reaction to Meropenem for Injection and Sodium Chloride Injection occurs, discontinue the drug immediately.

5.2 Severe Cutaneous Adverse Reactions

Severe cutaneous adverse reactions (SCAR) such as Stevens-Johnson syndrome (SJS), toxic epidermal necrolysis (TEN), drug reaction with eosinophilia and systemic symptoms (DRESS), erythema multiforme (EM) and acute generalized exanthematous pustulosis (AGEP) have been reported in patients receiving meropenem [see Adverse Reactions (6.2)]. If signs and symptoms suggestive of these reactions appear, Meropenem for Injection and Sodium Chloride Injection should be withdrawn immediately and an alternative treatment should be considered.

5.3 Rhabdomyolysis

Rhabdomyolysis has been reported with the use of meropenem [see Adverse Reactions (6.2)]. If signs or symptoms of rhabdomyolysis such as muscle pain, tenderness or weakness, dark urine, or elevated creatine phosphokinase are observed, discontinue Meropenem for Injection and Sodium Chloride Injection and initiate appropriate therapy.

5.4 Seizure Potential

Seizures and other adverse CNS experiences have been reported during treatment with meropenem for injection. These experiences have occurred most commonly in patients with CNS disorders (e.g., brain lesions or history of seizures) or with bacterial meningitis and/or compromised renal function [see Adverse Reactions (6.1) and Drug Interactions (7.2)].

During clinical investigations, 2904 immunocompetent adult patients were treated for non-CNS infections with the overall seizure rate being 0.7% (based on 20 patients with this adverse event). All meropenem-treated patients with seizures had pre-existing contributing factors. Among these are included prior history of seizures or CNS abnormality and concomitant medications with seizure potential. Dosage adjustment is recommended in patients with advanced age and/or adult patients with creatinine clearance of 50 mL/min or less [see Dosage and Administration (2.2)].

Close adherence to the recommended dosage regimens is urged, especially in patients with known factors that predispose to convulsive activity. Anti-convulsant therapy should be continued in patients with known seizure disorders. If focal tremors, myoclonus, or seizures occur, evaluate neurologically, place on anti-convulsant therapy if not already instituted, and re-examine the dosage of Meropenem for Injection and Sodium Chloride Injection to determine whether it should be decreased or discontinued.

5.5 Risk of Breakthrough Seizures Due to Drug Interaction with Valproic Acid

The concomitant use of meropenem and valproic acid or divalproex sodium is generally not recommended. Case reports in the literature have shown that co-administration of carbapenems, including meropenem, to patients receiving valproic acid or divalproex sodium results in a reduction in valproic acid concentrations. The valproic acid concentrations may drop below the therapeutic range as a result of this interaction, therefore increasing the risk of breakthrough seizures. Increasing the dose of valproic acid or divalproex sodium may not be sufficient to overcome this interaction. Consider administration of antibacterial drugs other than carbapenems to treat infections in patients whose seizures are well controlled on valproic acid or divalproex sodium. If administration of Meropenem for Injection and Sodium Chloride Injection is necessary, consider supplemental anti-convulsant therapy [see Drug Interactions (7.2)].

5.6 Clostridioides difficile–Associated Diarrhea

Clostridioides difficile-associated diarrhea (CDAD) has been reported with use of nearly all antibacterial agents, including meropenem for injection, and may range in severity from mild diarrhea to fatal colitis. Treatment with antibacterial agents alters the normal flora of the colon leading to overgrowth of C. difficile.

C. difficile produces toxins A and B which contribute to the development of CDAD. Hypertoxin producing isolates of C. difficile cause increased morbidity and mortality, as these infections can be refractory to antimicrobial therapy and may require colectomy. CDAD must be considered in all patients who present with diarrhea following antibacterial drug use. Careful medical history is necessary since CDAD has been reported to occur over two months after the administration of antibacterial agents.

If CDAD is suspected or confirmed, ongoing antibacterial drug use not directed against C. difficile may need to be discontinued. Appropriate fluid and electrolyte management, protein supplementation, antibacterial drug treatment of C. difficile, and surgical evaluation should be instituted as clinically indicated.

5.7 Development of Drug-Resistant Bacteria

Prescribing Meropenem for Injection and Sodium Chloride Injection in the absence of a proven or strongly suspected bacterial infection or a prophylactic indication is unlikely to provide benefit to the patient and increases the risk of the development of drug-resistant bacteria.

5.8 Overgrowth of Nonsusceptible Organisms

As with other broad-spectrum antibacterial drugs, prolonged use of meropenem may result in overgrowth of nonsusceptible organisms. Repeated evaluation of the patient is essential. If superinfection does occur during therapy, appropriate measures should be taken.

5.9 Thrombocytopenia

In patients with renal impairment, thrombocytopenia has been observed but no clinical bleeding reported [see Dosage and Administration (2.2), Adverse Reactions (6.1), Use In Specific Populations (8.5) and (8.6), and Clinical Pharmacology (12.3)].

5.10 Potential for Neuromotor Impairment

Alert patients receiving meropenem for injection on an outpatient basis regarding adverse events such as seizures, delirium, headaches and/or paresthesias that could interfere with mental alertness and/or cause motor impairment. Until it is reasonably well established that meropenem for injection is well tolerated, advise patients not to operate machinery or motorized vehicles [see Adverse Reactions (6.1)].

5.11 High Sodium Load

Each 500 mg of Meropenem for Injection and Sodium Chloride Injection delivers 245.1 mg (10.7 mEq) of sodium and each 1 gram of Meropenem for Injection and Sodium Chloride Injection delivers 290.2 mg (12.6 mEq) of sodium. Avoid use of Meropenem for Injection and Sodium Chloride Injection in patients with congestive heart failure, elderly patients and patients requiring restricted sodium intake.

6 ADVERSE REACTIONS

The following are discussed in greater detail in other sections of labeling:

- Hypersensitivity Reactions [see Warnings and Precautions (5.1)]
- Severe Cutaneous Adverse Reactions [see Warnings and Precautions (5.2)]
- Rhabdomyolysis [see Warnings and Precautions (5.3)]
- Seizure Potential [see Warnings and Precautions (5.4)]
- Risk of Breakthrough Seizures Due to Drug Interaction with Valproic Acid [see Warnings and Precautions (5.5)]
- Clostridioides difficile – Associated Diarrhea [see Warnings and Precautions (5.6)]
- Development of Drug-Resistant Bacteria [see Warnings and Precautions (5.7)]
- Overgrowth of Nonsusceptible Organisms [see Warnings and Precautions (5.8)]
- Thrombocytopenia [see Warnings and Precautions (5.9)]
- Potential for Neuromotor Impairment [see Warnings and Precautions (5.10)]
- High Sodium Load [see Warnings and Precautions (5.11)]

6.1 Adverse Reactions from Clinical Trials

Because clinical trials are conducted under widely varying conditions, adverse reactions rates observed in the clinical trials of a drug cannot be directly compared to rates in the clinical trials of another drug and may not reflect the rates observed in practice.

Adult Patients:

During clinical investigations, 2904 immunocompetent adult patients were treated for non-CNS infections with meropenem for injection (500 mg or 1000 mg every 8 hours). Deaths in 5 patients were assessed as possibly related to meropenem; 36 (1.2%) patients had meropenem discontinued because of adverse events. Many patients in these trials were severely ill and had multiple background diseases, physiological impairments and were receiving multiple other drug therapies.

In the seriously ill patient population, it was not possible to determine the relationship between observed adverse events and therapy with meropenem for injection.

The following adverse reaction frequencies were derived from the clinical trials in the 2904 patients treated with meropenem for injection.

Local Adverse Reactions

Local adverse reactions that were reported with meropenem for injection were as follows:

Inflammation at the injection site | 2.4%
Injection site reaction | 0.9%
Phlebitis/thrombophlebitis | 0.8%
Pain at the injection site | 0.4%
Edema at the injection site | 0.2%

Systemic Adverse Reactions

Systemic adverse events that were reported with meropenem for injection occurring in greater than 1.0% of the patients were diarrhea (4.8%), nausea/vomiting (3.6%), headache (2.3%), rash (1.9%), sepsis (1.6%), constipation (1.4%), apnea (1.3%), shock (1.2%), and pruritus (1.2%).

Additional systemic adverse reactions that were reported with meropenem for injection and occurring in less than or equal to 1.0% but greater than 0.1% of the patients are listed below within each body system in order of decreasing frequency:

Bleeding events were seen as follows: gastrointestinal hemorrhage (0.5%), melena (0.3%), epistaxis (0.2%), hemoperitoneum (0.2%).

Body as a Whole: pain, abdominal pain, chest pain, fever, back pain, abdominal enlargement, chills, pelvic pain

Cardiovascular: heart failure, heart arrest, tachycardia, hypertension, myocardial infarction, pulmonary embolus, bradycardia, hypotension, syncope

Digestive System: oral moniliasis, anorexia, cholestatic jaundice/jaundice, flatulence, ileus, hepatic failure, dyspepsia, intestinal obstruction

Hemic/Lymphatic: anemia, hypochromic anemia, hypervolemia

Metabolic/Nutritional: peripheral edema, hypoxia

Nervous System: insomnia, agitation, delirium, confusion, dizziness, seizure, nervousness, paresthesia, hallucinations, somnolence, anxiety, depression, asthenia [see Warnings and Precautions (5.4) and (5.10)]

Respiratory: respiratory disorder, dyspnea, pleural effusion, asthma, cough increased, lung edema

Skin and Appendages: urticaria, sweating, skin ulcer

Urogenital System: dysuria, kidney failure, vaginal moniliasis, urinary incontinence

Adverse Laboratory Changes

Adverse laboratory changes that were reported and occurring in greater than 0.2% of the patients were as follows:

Hepatic: increased alanine transaminase (ALT), aspartate transaminase (AST), alkaline phosphatase, lactate dehydrogenase (LDH), and bilirubin

Hematologic: increased platelets, increased eosinophils, decreased platelets, decreased hemoglobin, decreased hematocrit, decreased white blood cell (WBC), shortened prothrombin time and shortened partial thromboplastin time, leukocytosis, hypokalemia

Renal: increased creatinine and increased blood urea nitrogen (BUN)

Urinalysis: presence of red blood cells

Complicated Skin and Skin Structure Infections

In a study of complicated skin and skin structure infections, the adverse reactions were similar to those listed above. The most common adverse events occurring in greater than 5% of the patients were: headache (7.8%), nausea (7.8%), constipation (7.0%), diarrhea (7.0%), anemia (5.5%), and pain (5.1%). Adverse events with an incidence of greater than 1%, and not listed above, include: pharyngitis, accidental injury, gastrointestinal disorder, hypoglycemia, peripheral vascular disorder, and pneumonia.

Patients with Renal Impairment:

For patients with varying degrees of renal impairment, the incidence of heart failure, kidney failure, seizure and shock reported irrespective of relationship to meropenem for injection, increased in patients with moderately severe renal impairment (creatinine clearance greater than 10 to 26 mL/min) [see Dosage and Administration (2.2), Warnings and Precautions (5.9), Use in Specific Populations (8.5) and (8.6) and Clinical Pharmacology (12.3)].

Pediatric Patients

Systemic and Local Adverse Reactions

Pediatric Patients with Serious Bacterial Infections (excluding Bacterial Meningitis):

Meropenem for injection was studied in 515 pediatric patients (3 months of age and older to below 13 years of age) with serious bacterial infections (excluding meningitis, see next section) at dosages of 10 to 20 mg/kg every 8 hours. The types of systemic and local adverse events seen in these patients are similar to the adults, with the most common adverse events reported as possibly, probably, or definitely related to meropenem for injection and their rates of occurrence as follows:

Diarrhea | 3.5%
Rash | 1.6%
Nausea and Vomiting | 0.8%

Pediatric Patients with Bacterial Meningitis:

Meropenem for injection was studied in 321 pediatric patients (3 months of age and older to below 17 years of age) with meningitis at a dosage of 40 mg/kg every 8 hours. The types of systemic and local adverse events seen in these patients are similar to the adults, with the most common adverse events reported as possibly, probably, or definitely related to meropenem for injection and their rates of occurrence as follows:

Diarrhea | 4.7%
Rash (mostly diaper area moniliasis) | 3.1%
Oral Moniliasis | 1.9%
Glossitis | 1.0%

In the meningitis studies, the rates of seizure activity during therapy were comparable between patients with no CNS abnormalities who received meropenem and those who received comparator agents (either cefotaxime or ceftriaxone). In the meropenem for injection treated group, 12/15 patients with seizures had late onset seizures (defined as occurring on day 3 or later) versus 7/20 in the comparator arm. The meropenem group had a statistically higher number of patients with transient elevation of liver enzymes.

6.2 Post-Marketing Experience

The following adverse reactions have been identified during post-approval use of meropenem, including meropenem for injection. Because these reactions are reported voluntarily from a population of uncertain size, it is not always possible to reliably estimate their frequency or establish a causal relationship to drug exposure.

Worldwide post-marketing adverse reactions not otherwise listed in the Adverse Reactions from Clinical Trials section of this prescribing information and reported as possibly, probably, or definitely drug related are listed within each body system in order of decreasing severity.

Blood and Lymphatic System Disorders: agranulocytosis, neutropenia, and leukopenia; a positive direct or indirect Coombs test, and hemolytic anemia.

Immune System Disorders: angioedema.

Skin and Subcutaneous Disorders: toxic epidermal necrolysis (TEN), Stevens-Johnson syndrome (SJS), drug reaction with eosinophilia and systemic symptoms (DRESS), erythema multiforme (EM) and acute generalized exanthematous pustulosis (AGEP).

Musculoskeletal Disorders: rhabdomyolysis

7 DRUG INTERACTIONS

7.1 Probenecid

Probenecid competes with meropenem for active tubular secretion, resulting in increased plasma concentrations of meropenem. Coadministration of probenecid with meropenem is not recommended.

7.2 Valproic Acid

Case reports in the literature have shown that co-administration of carbapenems, including meropenem, to patients receiving valproic acid or divalproex sodium results in a reduction in valproic acid concentrations. The valproic acid concentrations may drop below the therapeutic range as a result of this interaction, therefore increasing the risk of breakthrough seizures. Although the mechanism of this interaction is unknown, data from in vitro and animal studies suggest that carbapenems may inhibit the hydrolysis of valproic acid’s glucuronide metabolite (VPA-g) back to valproic acid, thus decreasing the serum concentrations of valproic acid. If administration of meropenem for injection is necessary, then supplemental anti-convulsant therapy should be considered [see Warnings and Precautions (5.5)].

8 USE IN SPECIFIC POPULATIONS

8.1 Pregnancy

Risk Summary

There are insufficient human data to establish whether there is a drug-associated risk of major birth defects or miscarriages with meropenem in pregnant women.

No fetal toxicity or malformations were observed in pregnant rats and cynomolgus macaques administered intravenous meropenem during organogenesis at doses up to 3.2 and 2.3 times the maximum recommended human dose based on body surface area comparison, respectively. In rats administered intravenous meropenem in late pregnancy and during the lactation period, there were no adverse effects on offspring at doses equivalent to approximately 3.2 times the maximum recommended human dose based on body surface area comparison [see Data].

The background risk of major birth defects and miscarriage for the indicated population is unknown. In the U.S. general population, the estimated background risk of major birth defects and miscarriage in clinically recognized pregnancies is 2-4% and 15-20%, respectively.

Data

Animal Data

Reproductive studies have been performed with meropenem in rats at doses of up to 1000 mg/kg/day and in cynomolgus monkeys at doses of up to 360 mg/kg/day (on the basis of body surface area comparisons, approximately 3.2 times and 2.3 times higher, respectively, than the maximum recommended human dose of 1 gram every 8 hours). These studies revealed no evidence of harm to the fetus due to meropenem, although there were slight changes in fetal body weight at doses of 250 mg/kg/day (equivalent to approximately 0.8 times the maximum recommended human dose of 1 gram every 8 hours based on body surface area comparison) and above in rats. In a published study^2, meropenem administered to pregnant rats from Gestation Day 6 to Gestation Day 17, was associated with mild maternal weight loss at all doses, but did not produce malformations or fetal toxicity. The no-observed-adverse-effect-level (NOAEL) for fetal toxicity in this study was considered to be the high dose of 750 mg/kg/day (equivalent to approximately 2.4 times the highest recommended human dose based on body surface area comparison).

In a peri-postnatal study in rats described in the published literature^1, intravenous meropenem was administered to dams from Gestation Day 17 until Postpartum Day 21. There were no adverse effects in the dams and no adverse effects in the first generation offspring (including developmental, behavioral, and functional assessments and reproductive parameters) except that female offspring exhibited lowered body weights which continued during gestation and nursing of the second generation offspring. Second generation offspring showed no meropenem-related effects. The NOAEL value was considered to be 1000 mg/kg/day (approximately 3.2 times the highest recommended clinical dose based on body surface area comparisons).

8.2 Lactation

Risk Summary

Meropenem has been reported to be excreted in human milk. No information is available on the effects of meropenem on the breastfed –child or on milk production. The developmental and health benefits of breastfeeding should be considered along with the mother’s clinical need for Meropenem for Injection and Sodium Chloride Injection in the DUPLEX® Container and any potential adverse effects on the breastfed-child from Meropenem for Injection and Sodium Chloride Injection in the DUPLEX® Container or from the underlying maternal conditions.

8.4 Pediatric Use

Meropenem for Injection and Sodium Chloride Injection in the DUPLEX® Container is designed to deliver a 500 mg or 1 gram dose of meropenem. To prevent unintentional overdose, this product should not be used in pediatric patients who require less than the full adult dose of meropenem. Meropenem is not to be used in pediatric patients aged less than three months. [see Dosage and Administration (2.3)].

Use of meropenem for injection in pediatric patients with bacterial meningitis is supported by evidence from adequate and well-controlled studies in the pediatric population. Use of meropenem for injection in pediatric patients with intra-abdominal infections is supported by evidence from adequate and well-controlled studies with adults with additional data from pediatric pharmacokinetics studies and controlled clinical trials in pediatric patients. Use of meropenem for injection in pediatric patients with complicated skin and skin structure infections is supported by evidence from an adequate and well-controlled study with adults and additional data from pediatric pharmacokinetics studies [see Indications and Usage (1), Dosage and Administration (2.3), Adverse Reactions (6.1), Clinical Pharmacology (12.3) and Clinical Studies (14)].

8.5 Geriatric Use

Of the total number of subjects in clinical studies of meropenem for injection, approximately 1100 (30%) were 65 years of age and older, while 400 (11%) were 75 years and older. Additionally, in a study of 511 patients with complicated skin and skin structure infections, 93 (18%) were 65 years of age and older, while 38 (7%) were 75 years and older. No overall differences in safety or effectiveness were observed between these subjects and younger subjects; spontaneous reports and other reported clinical experience have not identified differences in responses between the elderly and younger patients, but greater sensitivity of some older individuals cannot be ruled out.

Meropenem is known to be substantially excreted by the kidney, and the risk of adverse reactions to this drug may be greater in patients with renal impairment. Because elderly patients are more likely to have decreased renal function, care should be taken in dose selection, and it may be useful to monitor renal function.

A pharmacokinetic study with meropenem for injection in elderly patients has shown a reduction in the plasma clearance of meropenem that correlates with age-associated reduction in creatinine clearance [see Clinical Pharmacology (12.3)].

Each 500 mg of Meropenem for Injection and Sodium Chloride Injection delivers 245.1 mg (10.7 mEq) of sodium and each 1 gram of Meropenem for Injection and Sodium Chloride Injection delivers 290.2 mg (12.6 mEq) of sodium. At the usual recommended doses of 500 mg or 1000 mg every 8 hours, patients would receive between 735 mg/day and 870 mg/day (32 mEq and 38 mEq) of sodium. The geriatric population may respond with a blunted natriuresis to salt loading. This may be clinically important with regard to such diseases as congestive heart failure [see Contraindications (4) and Warnings and Precautions (5.11)].

8.6 Patients with Renal Impairment

Dosage adjustment is necessary in patients with creatinine clearance 50 mL/min or less [see Dosage and Administration (2.2), Warnings and Precautions (5.9), and Clinical Pharmacology (12.3)].

10 OVERDOSAGE

In mice and rats, large intravenous doses of meropenem (2200-4000 mg/kg) have been associated with ataxia, dyspnea, convulsions, and mortalities.

Intentional overdosing of Meropenem for Injection and Sodium Chloride Injection is unlikely, although accidental overdosing might occur if large doses are given to patients with reduced renal function. The largest dose of meropenem administered in clinical trials has been 2 grams given intravenously every 8 hours. At this dosage, no adverse pharmacological effects or increased safety risks have been observed.

Limited post-marketing experience indicates that if adverse events occur following overdosage, they are consistent with the adverse event profile described in the Adverse Reactions section and are generally mild in severity and resolve on withdrawal or dose reduction. Symptomatic treatments should be considered. In individuals with normal renal function, rapid renal elimination takes place. Meropenem and its metabolite are readily dialyzable and effectively removed by hemodialysis; however, no information is available on the use of hemodialysis to treat overdosage.

11 DESCRIPTION

Meropenem for injection is a sterile, pyrogen-free, synthetic, carbapenem antibacterial drug for intravenous administration. Meropenem is (4R,5S,6S)-3- [[(3S,5S)-5-(Dimethylcarbamoyl)-3-pyrrolidinyl]thio]-6-[(1R)-1-hydroxyethyl]-4-methyl-7-oxo-1-azabicyclo[3.2.0]hept-2-ene-2-carboxylic acid trihydrate. Its empirical formula is C17H25N3O5S•3H2O with a molecular weight of 437.52.

Its structural formula is:

Meropenem for injection is a white to pale yellow crystalline powder containing meropenem trihydrate and sodium carbonate. The constituted solution varies from colorless to yellow depending on the concentration. The pH of freshly constituted solutions is between 7.3 and 8.3. Meropenem is soluble in 5% monobasic potassium phosphate solution, sparingly soluble in water, very slightly soluble in hydrated ethanol, and practically insoluble in acetone or ether.

Meropenem for Injection USP and Sodium Chloride Injection USP is supplied as a sterile, nonpyrogenic, single-dose packaged combination of meropenem (drug chamber) and 50 mL of sodium chloride (diluent) in the DUPLEX® sterile container. When reconstituted as instructed, each 1 gram Meropenem for injection in the DUPLEX® Container will deliver 1 gram of meropenem and a total sodium content of 290.2 mg (12.6 mEq). Each 500 mg Meropenem for injection in the DUPLEX® Container will deliver 500 mg of meropenem and a total sodium content of 245.1 mg (10.7 mEq) [see Dosage and Administration (2.4)]. The osmolality of the reconstituted solution of Meropenem for Injection USP and Sodium Chloride Injection USP is approximately 356 mOsmol/kg for the 500 mg dose and approximately 417 mOsmol/kg for the 1 gram dose.

The DUPLEX® Container is a flexible dual chamber container. After removing the peelable foil strip, activating the seals, and thoroughly mixing, the reconstituted drug product is hyperosmotic and is intended for single intravenous use. The product (diluent and drug) contact layer is a mixture of thermoplastic rubber and a polypropylene ethylene copolymer that contains no plasticizers.

Not made with natural rubber latex, PVC or Di(2-ethylhexyl)phthalate (DEHP).

12 CLINICAL PHARMACOLOGY

12.1 Mechanism of Action

Meropenem is an antibacterial drug [see Microbiology (12.4)].

12.2 Pharmacodynamics

The percentage of time of a dosing interval that unbound plasma concentration of meropenem exceeds the meropenem minimum inhibitory concentration (MIC) against the infecting organism has been shown to best correlate with efficacy in animal and in vitro models of infection.

12.3 Pharmacokinetics

Plasma Concentrations

At the end of a 30-minute intravenous infusion of a single dose of meropenem for injection in healthy volunteers, mean peak plasma concentrations of meropenem are approximately 23 mcg/mL (range 14-26) for the 500 mg dose and 49 mcg/mL (range 39-58) for the 1 gram dose. A 5-minute intravenous bolus injection of meropenem in healthy volunteers results in mean peak plasma concentrations of approximately 45 mcg/mL (range 18-65) for the 500 mg dose and 112 mcg/mL (range 83-140) for the 1 gram dose.

Following intravenous doses of 500 mg, mean plasma concentrations of meropenem usually decline to approximately 1 mcg/mL at 6 hours after administration.

No accumulation of meropenem in plasma was observed with regimens using 500 mg administered every 8 hours or 1 gram administered every 6 hours in healthy volunteers with normal renal function.

Distribution

The plasma protein binding of meropenem is approximately 2%.

After a single intravenous dose of meropenem for injection, the highest mean concentrations of meropenem were found in tissues and fluids at 1 hour (0.5 to 1.5 hours) after the start of infusion, except where indicated in the tissues and fluids listed in table 3 below.

Table 3: Meropenem Concentrations in Selected Tissues (Highest Concentrations Reported)

Tissue | Intravenous Dose (gram) | Number of Samples | Mean [mcg/mL or mcg/(g)] [at 1 hour unless otherwise noted] | Range [mcg/mL or mcg/(g)]
Endometrium | 0.5 | 7 | 4.2 | 1.7–10.2
Myometrium | 0.5 | 15 | 3.8 | 0.4–8.1
Ovary | 0.5 | 8 | 2.8 | 0.8–4.8
Cervix | 0.5 | 2 | 7 | 5.4–8.5
Fallopian tube | 0.5 | 9 | 1.7 | 0.3-3.4
Skin | 0.5 | 22 | 3.3 | 0.5–12.6
Interstitial fluid [obtained from blister fluid] | 0.5 | 9 | 5.5 | 3.2-8.6
Skin | 1 | 10 | 5.3 | 1.3–16.7
Interstitial fluid | 1 | 5 | 26.3 | 20.9–37.4
Colon | 1 | 2 | 2.6 | 2.5–2.7
Bile | 1 | 7 | 14.6 (3 hours) | 4.0–25.7
Gall bladder | 1 | 1 | — | 3.9
Peritoneal fluid | 1 | 9 | 30.2 | 7.4–54.6
Lung | 1 | 2 | 4.8 (2 hours) | 1.4–8.2
Bronchial mucosa | 1 | 7 | 4.5 | 1.3–11.1
Muscle | 1 | 2 | 6.1 (2 hours) | 5.3–6.9
Fascia | 1 | 9 | 8.8 | 1.5–20
Heart valves | 1 | 7 | 9.7 | 6.4–12.1
Myocardium | 1 | 10 | 15.5 | 5.2–25.5
CSF (inflamed) | 20 mg/kg [in pediatric patients of age 5 months to 8 years] | 8 | 1.1 (2 hours) | 0.2-2.8
CSF (inflamed) | 40 mg/kg [in pediatric patients of age 1 month to 15 years] | 5 | 3.3 (3 hours) | 0.9-6.5
CSF (uninflamed) | 1 | 4 | 0.2 (2 hours) | 0.1–0.3

Elimination

In subjects with normal renal function, the elimination half-life of meropenem is approximately 1 hour.

Metabolism

There is one metabolite of meropenem that is microbiologically inactive.

Excretion

Meropenem is primarily excreted unchanged by the kidneys. Approximately 70% (50 – 75%) of the dose is excreted unchanged within 12 hours. A further 28% is recovered as the microbiologically inactive metabolite. Fecal elimination represents only approximately 2% of the dose. The measured renal clearance and the effect of probenecid show that meropenem undergoes both filtration and tubular secretion.

Urinary concentrations of meropenem in excess of 10 mcg/mL are maintained for up to 5 hours after a 500 mg dose.

Specific Populations

Patients with Renal Impairment

Pharmacokinetic studies with meropenem for injection in patients with renal impairment have shown that the plasma clearance of meropenem correlates with creatinine clearance. Dosage adjustments are necessary in subjects with renal impairment (creatinine clearance 50 mL/min or less) [see Dosage and Administration (2.2) and Use In Specific Populations (8.6)].

Meropenem is hemodialyzable. However, there is no information on the usefulness of hemodialysis to treat overdosage [see Overdosage (10)].

Patients with Hepatic Impairment

A pharmacokinetic study with meropenem for injection in patients with hepatic impairment has shown no effects of liver disease on the pharmacokinetics of meropenem.

Geriatric Patients

A pharmacokinetic study with meropenem for injection in elderly patients with renal impairment showed a reduction in plasma clearance of meropenem that correlates with age-associated reduction in creatinine clearance.

Pediatric Patients

The pharmacokinetics of meropenem in pediatric patients 2 years of age or older are similar to those in adults. The elimination half-life for meropenem was approximately 1.5 hours in pediatric patients of age 3 months to 2 years.

The pharmacokinetics of meropenem in patients less than 3 months of age receiving combination antibacterial drug therapy are given below.

Table 4: Meropenem Pharmacokinetic Parameters in Patients Less Than 3 Months of Age [Values are derived from a population pharmacokinetic analysis of sparse data]

 | GA less than 32 weeks PNA less than 2 weeks (20mg/kg every 12 hours) | GA less than 32 weeks PNA 2 weeks or older (20mg/kg every 8 hours) | GA 32 weeks or older PNA less than 2 weeks (20mg/kg every 8 hours) | GA 32 weeks or older PNA 2 weeks or older (30mg/kg every 8 hours) | Overall
CL (L/h/kg) | 0.089 | 0.122 | 0.135 | 0.202 | 0.119
V (L/kg) | 0.489 | 0.467 | 0.463 | 0.451 | 0.468
AUC0-24 (mcg-h/mL) | 448 | 491 | 445 | 444 | 467
Cmax (mcg/mL) | 44.3 | 46.5 | 44.9 | 61 | 46.9
Cmin (mcg/mL) | 5.36 | 6.65 | 4.84 | 2.1 | 5.65
T1/2 (h) | 3.82 | 2.68 | 2.33 | 1.58 | 2.68

Drug Interactions

Probenecid competes with meropenem for active tubular secretion and thus inhibits the renal excretion of meropenem. Following administration of probenecid with meropenem, the mean systemic exposure increased 56% and the mean elimination half-life increased 38%. Co-administration of probenecid with meropenem is not recommended.

12.4 Microbiology

Mechanism of Action

The bactericidal activity of meropenem results from the inhibition of cell wall synthesis. Meropenem penetrates the cell wall of most Gram-positive and Gram-negative bacteria to reach penicillin-binding-protein (PBP) targets. Meropenem binds to PBPs 2, 3 and 4 of Escherichia coli and Pseudomonas aeruginosa; and PBPs 1, 2 and 4 of Staphylococcus aureus. Bactericidal concentrations (defined as a 3 log10 reduction in cell counts within 12 to 24 hours) are typically 1-2 times the bacteriostatic concentrations of meropenem, with the exception of Listeria monocytogenes, against which lethal activity is not observed.

Meropenem has significant stability to hydrolysis by beta-lactamases, both penicillinases and cephalosporinases produced by Gram-positive and Gram-negative bacteria.

Meropenem does not have in-vitro activity against methicillin-resistant Staphylococcus aureus (MRSA) or methicillin-resistant Staphylococcus epidermidis (MRSE).

Resistance

There are several mechanisms of resistance to carbapenems: 1) decreased permeability of the outer membrane of Gram-negative bacteria (due to diminished production of porins) causing reduced bacterial uptake, 2) reduced affinity of the target PBPs, 3) increased expression of efflux pump components, and 4) production of antibacterial drug-destroying enzymes (carbapenemases, metallo-beta-lactamases).

Cross-Resistance

Cross-resistance is sometimes observed with isolates resistant to other carbapenems.

Interaction with Other Antimicrobials

In vitro tests show meropenem to act synergistically with aminoglycoside antibacterial drugs against some isolates of Pseudomonas aeruginosa.

Antimicrobial Activity

Meropenem has been shown to be active against most isolates of the following microorganisms, both in vitro and in clinical infections [see Indications and Usage (1)].

Gram-positive bacteria

- Enterococcus faecalis (vancomycin-susceptible isolates only)
- Staphylococcus aureus (methicillin-susceptible isolates only)
- Streptococcus agalactiae
- Streptococcus pneumoniae (penicillin-susceptible isolates only)
- Streptococcus pyogenes
- Viridans group streptococci

Gram-negative bacteria

- Escherichia coli
- Haemophilus influenzae
- Klebsiella pneumoniae
- Neisseria meningitidis
- Proteus mirabilis
- Pseudomonas aeruginosa

Anaerobic bacteria

- Bacteroides fragilis
- Bacteroides thetaiotaomicron
- Peptostreptococcus species

The following in vitro data are available, but their clinical significance is unknown. At least 90 percent of the following bacteria exhibit an in vitro minimum inhibitory concentration (MIC) less than or equal to the susceptible breakpoint for meropenem against isolates of similar genus or organism group. However, the efficacy of meropenem in treating clinical infections caused by these microorganisms has not been established in adequate and well-controlled clinical trials.

Gram-positive bacteria

- Staphylococcus epidermidis (methicillin-susceptible isolates only)

Gram-negative bacteria

- Aeromonas hydrophila
- Campylobacter jejuni
- Citrobacter freundii
- Citrobacter koseri
- Enterobacter cloacae
- Hafnia alvei
- Klebsiella oxytoca
- Moraxella catarrhalis
- Morganella morganii
- Pasteurella multocida
- Proteus vulgaris
- Serratia marcescens

Anaerobic bacteria

- Bacteroides ovatus
- Bacteroides uniformis
- Bacteroides ureolyticus
- Bacteroides vulgatus
- Clostridioides difficile
- Clostridium perfringens
- Eggerthella lenta
- Fusobacterium species
- Parabacteroides distasonis
- Porphyromonas asaccharolytica
- Prevotella bivia
- Prevotella intermedia
- Prevotella melaninogenica
- Propionibacterium acnes

Susceptibility Test Methods

For specific information regarding susceptibility test interpretive criteria, and associated test methods and quality control standards recognized by FDA for this drug, please see: http://www.fda.gov/STIC.

13 NONCLINICAL TOXICOLOGY

13.1 Carcinogenesis, Mutagenesis, Impairment of Fertility

Carcinogenesis:

Carcinogenesis studies have not been performed.

Mutagenesis:

Genetic toxicity studies were performed with meropenem using the bacterial reverse mutation test, the Chinese hamster ovary HGPRT assay, cultured human lymphocytes cytogenic assay, and the mouse micronucleus test. There was no evidence of mutagenic potential found in any of these tests.

Impairment of Fertility:

Reproductive studies performed with meropenem in rats at doses up to 1000 mg/kg/day, (approximately 1.8 times the human exposure at a dose of 1 gram every 8 hours based on AUC) showed no evidence of fertility impairment.

14 CLINICAL STUDIES

14.1 Complicated Skin and Skin Structure Infections

Adult patients with complicated skin and skin structure infections including complicated cellulitis, complex abscesses, perirectal abscesses, and skin infections requiring intravenous antimicrobials, hospitalization, and surgical intervention were enrolled in a randomized, multi-center, international, double-blind trial. The study evaluated meropenem at doses of 500 mg administered intravenously every 8 hours and imipenem-cilastatin at doses of 500 mg administered intravenously every 8 hours. The study compared the clinical response between treatment groups in the clinically evaluable population at the follow-up visit (test-of-cure). The trial was conducted in the United States, South Africa, Canada, and Brazil. At enrollment, approximately 37% of the patients had underlying diabetes, 12% had underlying peripheral vascular disease and 67% had a surgical intervention. The study included 510 patients randomized to meropenem and 527 patients randomized to imipenem-cilastatin. Two hundred and sixty one (261) patients randomized to meropenem and 287 patients randomized to imipenem-cilastatin were clinically evaluable. The success rates in the clinically evaluable patients at the follow-up visit were 86% (225/261) in the meropenem arm and 83% (238/287) in imipenem-cilastatin arm.

The success rates for clinically evaluable population are provided in Table 5.

Table 5: Success Rates at Test-of-Cure Visit for Clinically Evaluable Population with Complicated Skin and Skin Structure Infections

Population | Meropenem for Injection n [n=number of patients with satisfactory response.] /N [N=number of patients in the clinically evaluable population or respective subgroup within treatment groups.] (%) | Imipenem-cilastatin n/N(%)
Total | 225/261 (86) | 238/287 (83)
Diabetes mellitus | 83/97 (86) | 76/105 (72)
No diabetes mellitus | 142/164 (87) | 162/182 (89)
Less than 65 years of age | 190/218 (87) | 205/241 (85)
65 years of age and older | 35/43 (81) | 33/46 (72)
Men | 130/148 (88) | 137/172 (80)
Women | 95/113 (84) | 101/115 (88)

The clinical efficacy rates by pathogen are provided in Table 6. The values represent the number of patients clinically cured/number of clinically evaluable patients at the post-treatment follow-up visit, with the percent cure in parentheses (Fully Evaluable analysis set).

Table 6: Clinical Efficacy Rates by Pathogen for Clinically Evaluable Population

MICROORGANISMS [Patients may have more than one pretreatment pathogen.] | Meropenem for Injection n [n=number of patients with satisfactory response.] /N [N=number of patients in the clinically evaluable population or subgroup within treatment groups.] (%) [%= Percent of satisfactory clinical response at follow-up evaluation.] | Imipenem-cilastatin n/N (%)
Gram-positive aerobes
Staphylococcus aureus, methicillin susceptible | 82/88 (93) | 84/100 (84)
Streptococcus pyogenes (Group A) | 26/29 (90) | 28/32 (88)
Streptococcus agalactiae (Group B) | 12/17 (71) | 16/19 (84)
Enterococcus faecalis | 9/12 (75) | 14/20 (70)
Viridans group streptococci | 11/12 (92) | 5/6 (83)
Gram-negative aerobes
Escherichia coli | 12/15 (80) | 15/21 (71)
Pseudomonas aeruginosa | 11/15 (73) | 13/15 (87)
Proteus mirabilis | 11/13 (85) | 6/7 (86)
Anaerobes
Bacteroides fragilis | 10/11 (91) | 9/10 (90)
Peptostreptococcus spp. | 10/13 (77) | 14/16 (88)

The proportion of patients who discontinued study treatment due to an adverse event was similar for both treatment groups (meropenem, 2.5% and imipenem-cilastatin, 2.7%).

14.2 Complicated Intra-Abdominal Infections

One controlled clinical study of complicated intra-abdominal infection was performed in the United States where meropenem was compared with clindamycin/tobramycin. Three controlled clinical studies of complicated intra-abdominal infections were performed in Europe; meropenem was compared with imipenem (two trials) and cefotaxime/metronidazole (one trial).

Using strict evaluability criteria and microbiologic eradication and clinical cures at follow-up which occurred 7 or more days after completion of therapy, the presumptive microbiologic eradication/clinical cure rates and statistical findings are provided in Table 7.

Table 7: Presumptive Microbiologic Eradication and Clinical Cure Rates at Test-of-Cure Visit in the Evaluable population with Complicated intra-abdominal infections

Treatment Arm | No. evaluable/ No. enrolled (%) | Microbiologic Eradication Rate | Clinical Cure Rate | Outcome
meropenem | 146/516 (28%) | 98/146 (67%) | 101/146 (69%)
imipenem | 65/220 (30%) | 40/65 (62%) | 42/65 (65%) | Meropenem equivalent to control
cefotaxime/metronidazole | 26/85 (30%) | 22/26 (85%) | 22/26 (85%) | Meropenem not equivalent to control
clindamycin/tobramycin | 50/212 (24%) | 38/50 (76%) | 38/50 (76%) | Meropenem equivalent to control

The finding that meropenem was not statistically equivalent to cefotaxime/metronidazole may have been due to uneven assignment of more seriously ill patients to the meropenem arm. Currently there is no additional information available to further interpret this observation.

14.3 Bacterial Meningitis

Four hundred forty-six patients (397 pediatric patients 3 months of age and older to below 17 years of age) were enrolled in 4 separate clinical trials and randomized to treatment with meropenem (n=225) at a dose of 40 mg/kg every 8 hours or a comparator drug, i.e., cefotaxime (n=187) or ceftriaxone (n=34), at the approved dosing regimens. A comparable number of patients were found to be clinically evaluable (ranging from 61-68%) and with a similar distribution of pathogens isolated on initial CSF culture.

Patients were defined as clinically not cured if any one of the following three criteria were met:

1. At the 5-7 week post-completion of therapy visit, the patient had any one of the following: moderate to severe motor, behavior or development deficits, hearing loss of greater than 60 decibels in one or both ears, or blindness.
2. During therapy the patient’s clinical status necessitated the addition of other antibacterial drugs.
3. Either during or post-therapy, the patient developed a large subdural effusion needing surgical drainage, or a cerebral abscess, or a bacteriologic relapse.

Using the definition, the following efficacy rates were obtained, per organism (noted in Table 8). The values represent the number of patients clinically cured/number of clinically evaluable patients, with the percent cure in parentheses.

Table 8: Efficacy Rates by Pathogen in the Clinically Evaluable Population with Bacterial Meningitis

MICROORGANISMS | MEROPENEM FOR INJECTION | COMPARATOR
S. pneumoniae | 17/24 (71) | 19/30 (63)
H. influenzae (+) [(+) beta-lactamase-producing] | 8/10 (80) | 6/6 (100)
H. influenzae (-/NT) [(-/NT) non-beta-lactamase-producing or not tested] | 44/59 (75) | 44/60 (73)
N. meningitidis | 30/35 (86) | 35/39 (90)
Total (including others) | 102/131 (78) | 108/140 (77)

Sequelae were the most common reason patients were assessed as clinically not cured.

Five patients were found to be bacteriologically not cured, 3 in the comparator group (1 relapse and 2 patients with cerebral abscesses) and 2 in the meropenem group (1 relapse and 1 with continued growth of Pseudomonas aeruginosa).

With respect to hearing loss, 263 of the 271 evaluable patients had at least one hearing test performed post-therapy. The following table shows the degree of hearing loss between the meropenem-treated patients and the comparator-treated patients.

Table 9: Hearing Loss at Post-Therapy in the Evaluable Population treated with Meropenem

Degree of Hearing Loss (in one or both ears) | Meropenem n = 128 | Comparator n = 135
No loss | 61% | 56%
20-40 decibels | 20% | 24%
greater than 40-60 decibels | 8% | 7%
greater than 60 decibels | 9% | 10%

15 REFERENCES

1. Cockcroft DW, MH Gault, 1976, Prediction of creatinine clearance from serum creatinine, Nephron, 16:31-41.
2. Kawamura S, AW Russell, SJ Freeman, and RA Siddall, 1992, Reproductive and Developmental Toxicity of Meropenem in Rats, Chemotherapy, 40:S238-250.

16 HOW SUPPLIED/STORAGE AND HANDLING

Meropenem for Injection USP and Sodium Chloride Injection USP in the DUPLEX® Container is a flexible dual chamber single-dose container supplied in two concentrations. The diluent chamber contains approximately 50 mL of 0.9% Sodium Chloride Injection USP. After reconstitution, the delivered doses are equivalent to 500 [Anhydrous basis.] mg and 1 gram meropenem.

Meropenem for Injection USP and Sodium Chloride Injection USP is supplied sterile and nonpyrogenic in the DUPLEX® Container packaged 24 units per case.

NDC | REF | Dose | Volume
0264-3183-11 | 3183-11 | 500 mg | 50 mL
0264-3185-11 | 3185-11 | 1 gram | 50 mL

Store the unactivated unit at 20°C–25°C (68°F–77°F). Excursion permitted to 15°C-30°C. [See USP Controlled Room Temperature.] Protect from freezing.

Use only if prepared solution is clear and free from particulate matter.

17 PATIENT COUNSELING INFORMATION

- Patients should be counseled that antibacterial drugs including Meropenem for Injection and Sodium Chloride Injection should only be used to treat bacterial infections. They do not treat viral infections (e.g., the common cold). When Meropenem for Injection and Sodium Chloride Injection is prescribed to treat a bacterial infection, patients should be told that although it is common to feel better early in the course of therapy, the medication should be taken exactly as directed. Skipping doses or not completing the full course of therapy may (1) decrease the effectiveness of the immediate treatment and (2) increase the likelihood that bacteria will develop resistance and will not be treatable by Meropenem for Injection and Sodium Chloride Injection or other antibacterial drugs in the future.
- Counsel patients that diarrhea is a common problem caused by antibacterial drugs which usually ends when the antibacterial drug is discontinued. Sometimes after starting treatment with antibacterial drugs, patients can develop watery and bloody stools (with or without stomach cramps and fever) even as late as two or more months after having taken the last dose of the antibacterial drug. If this occurs, patients should contact their physician as soon as possible [see Warnings and Precautions (5.6)].
- Counsel patients to inform their physician if they are taking valproic acid or divalproex sodium. Valproic acid concentrations in the blood may drop below the therapeutic range upon co-administration with Meropenem for Injection and Sodium Chloride Injection. If treatment with Meropenem for Injection and Sodium Chloride Injection is necessary and continued, alternative or supplemental anti-convulsant medication to prevent and/or treat seizures may be needed [see Warnings and Precautions (5.5)].
- Patients receiving Meropenem for Injection and Sodium Chloride Injection on an outpatient basis must be alerted of adverse events such as seizures, delirium, headaches and/or paresthesias that could interfere with mental alertness and/or cause motor impairment. Until it is reasonably well established that Meropenem for Injection and Sodium Chloride Injection is well tolerated, patients should not operate machinery or motorized vehicles [see Warnings and Precautions (5.10)].
- Meropenem for Injection and Sodium Chloride Injection contains a high sodium load. Instruct patients to inform or report symptoms of difficulty breathing, swelling, or increased weight [see Warnings and Precautions (5.11)].

DUPLEX is a registered trademark of B. Braun Medical Inc.
ATCC is a registered trademark of the American Type Culture Collection

Manufactured for:
B. Braun Medical Inc.
Bethlehem, PA 18018-3524 USA
1-800-227-2862

Manufactured by:
ACS Dobfar S.p.A.
Prepared in Italy. API from Italy and Austria.

Y36-003-091 LD-244-5

PRINCIPAL DISPLAY PANEL - 500 mg

Meropenem for Injection USP
and Sodium Chloride Injection USP

500 mg*

50 mL

NDC 0264-3183-11

DUPLEX® CONTAINER

USE ONLY AFTER MIXING CONTENTS OF BOTH CHAMBERS.

FOR INTRAVENOUS INFUSION ONLY

SINGLE-DOSE

* Contains sterile meropenem trihydrate USP equivalent to 500 mg of meropenem activity and sodium carbonate as a buffering agent.

Hyperosmotic Sterile/Nonpyrogenic

After reconstitution each 50 mL single-dose DUPLEX® unit contains Meropenem for Injection USP (equivalent to 500 mg meropenem) and a total sodium content of 245.1 mg (10.7 mEq). Approximate osmolality: 356 mOsmol/kg

Prior to Reconstitution: Store at 20°C-25°C (68°F-77°F). [See USP Controlled Room Temperature.] Use only if container and seals are intact. Do not peel foil strip until ready for use. After foil strip removal, product must be used within 7 days, but not beyond the labeled expiration date. Protect from light after removal of foil strip.

Reconstitution: Hold container with set port in a downward direction and fold the diluent chamber just below the solution meniscus. To activate seal, squeeze folded diluent chamber until seal between diluent and drug chamber opens, releasing diluent into drug chamber. Agitate the reconstituted solution until the drug powder is completely dissolved. Fold the container a second time and squeeze until seal between drug chamber and set port opens.

After Reconstitution: Use only if prepared solution is clear and free from particulate matter. Use within 1 hour if stored at room temperature or within 15 hours if stored under refrigeration. Do not use in a series connection. Do not introduce additives into this container. Prior to administration check for minute leaks by squeezing container firmly. If leaks are found, discard container and solution as sterility may be impaired. Do not freeze. Discard unused portion.

Not made with natural rubber latex, PVC or DEHP.

REF 3183-11

Rx only

E113USMERO502

Manufactured for:
B. Braun Medical Inc.

Prepared in Italy. API from Italy and Austria.

Y37-002-563 LD-440-4

EXP

LOT

PRINCIPAL DISPLAY PANEL - 1 g

Meropenem for Injection USP
and Sodium Chloride Injection USP

1 g*

50 mL

NDC 0264-3185-11

DUPLEX® CONTAINER

USE ONLY AFTER MIXING CONTENTS OF BOTH CHAMBERS.

FOR INTRAVENOUS INFUSION ONLY

SINGLE-DOSE

* Contains sterile meropenem trihydrate USP equivalent to 1 g of meropenem activity and sodium carbonate as a buffering agent.

Hyperosmotic Sterile/Nonpyrogenic

After reconstitution each 50 mL single-dose DUPLEX® unit contains Meropenem for Injection USP (equivalent to 1 g meropenem) and a total sodium content of 290.2 mg (12.6 mEq). Approximate osmolality: 417 mOsmol/kg

Prior to Reconstitution: Store at 20°C-25°C (68°F-77°F). [See USP Controlled Room Temperature.] Use only if container and seals are intact. Do not peel foil strip until ready for use. After foil strip removal, product must be used within 7 days, but not beyond the labeled expiration date. Protect from light after removal of foil strip.

Reconstitution: Hold container with set port in a downward direction and fold the diluent chamber just below the solution meniscus. To activate seal, squeeze folded diluent chamber until seal between diluent and drug chamber opens, releasing diluent into drug chamber. Agitate the reconstituted solution until the drug powder is completely dissolved. Fold the container a second time and squeeze until seal between drug chamber and set port opens.

After Reconstitution: Use only if prepared solution is clear and free from particulate matter. Use within 1 hour if stored at room temperature or within 15 hours if stored under refrigeration. Do not use in a series connection. Do not introduce additives into this container. Prior to administration check for minute leaks by squeezing container firmly. If leaks are found, discard container and solution as sterility may be impaired. Do not freeze. Discard unused portion.

Not made with natural rubber latex, PVC or DEHP.

REF 3185-11

Rx only

E113USMERO102

Manufactured for:
B. Braun Medical Inc.

Prepared in Italy. API from Italy and Austria.

Y37-002-564 LD-439-4

EXP

LOT

PACKAGE LABEL

PEEL HERE

Drug Chamber
Discard unit if foil strip is damaged. Peel foil strip only when ready for use. Visually inspect drug prior to reconstitution.

See package insert for complete directions for reconstitution and administration.

LD-336-1 X27-001-485